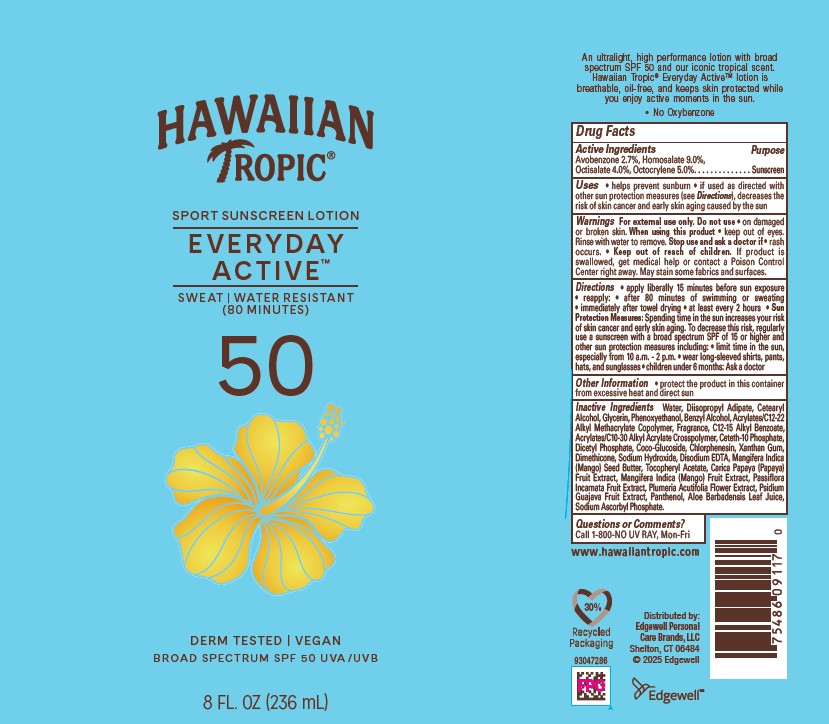 DRUG LABEL: Hawaiian Tropic Everyday Active SPF50
NDC: 63354-179 | Form: LOTION
Manufacturer: Edgewell Personal Care Brands LLC
Category: otc | Type: HUMAN OTC DRUG LABEL
Date: 20251231

ACTIVE INGREDIENTS: AVOBENZONE 2.7 g/100 g; HOMOSALATE 9 g/100 g; OCTOCRYLENE 5 g/100 g; OCTISALATE 4 g/100 g
INACTIVE INGREDIENTS: XANTHAN GUM; MANGO; PANTHENOL; SODIUM HYDROXIDE; EDETATE DISODIUM ANHYDROUS; PHENOXYETHANOL; PASSIFLORA INCARNATA FRUIT; CETETH-10 PHOSPHATE; PAPAYA; WATER; CETOSTEARYL ALCOHOL; BENZYL ALCOHOL; ALKYL (C12-15) BENZOATE; COCO GLUCOSIDE; CHLORPHENESIN; DIMETHICONE; MANGIFERA INDICA SEED BUTTER; PLUMERIA RUBRA FLOWER; GUAVA; ALOE VERA LEAF; SODIUM ASCORBYL PHOSPHATE; DIISOPROPYL ADIPATE; DIHEXADECYL PHOSPHATE; .ALPHA.-TOCOPHEROL ACETATE; GLYCERIN

Active Ingredients

Avobenzone 2.7%, Homosalate 9.0%, Octisalate 4.0%, Octocrylene 5.0%

Purpose

Sunscreen

Uses

• helps prevent sunburn • if used as directed with other sun protection measures (see Directions), decreases the risk of skin cancer and early skin aging caused by the sun

Warnings

For external use only

May stain some fabrics and surfaces

Do not use

on damaged or broken skin

When using this product

do not get into eyes. If contact occurs, rinse thoroughly with water

Stop use and ask a doctor

if irritation or rash develops.

Keep out of reach of children.

If swallowed, get medical help or contact a Poison Control Center right away.

Directions

apply liberally 15 minutes before sun exposure • reapply: • after 80 minutes of swimming or sweating • immediately after towel drying • at least every 2 hours • Sun Protection Measures: Spending time in the sun increases your risk of skin cancer and early skin aging. To decrease this risk, regularly use a sunscreen with a broad spectrum SPF of 15 or higher and other sun protection measures including: • limit time in the sun, especially from 10 a.m. - 2 p.m. • wear long-sleeved shirts, pants, hats, and sunglasses • children under 6 months: Ask a doctor

Inactive Ingredients

Water, Diisopropyl Adipate, Cetearyl Alcohol, Glycerin, Phenoxyethanol, Benzyl Alcohol, Acrylates/C12-22 Alkyl Methacrylate Copolymer, Fragrance, C12-15 Alkyl Benzoate, Acrylates/C10-30 Alkyl Acrylate Crosspolymer, Ceteth-10 Phosphate, Dicetyl Phosphate, Coco-Glucoside, Chlorphenesin, Xanthan Gum, Dimethicone, Sodium Hydroxide, Disodium EDTA, Mangifera Indica (Mango) Seed Butter, Tocopheryl Acetate, Carica Papaya (Papaya) Fruit Extract, Mangifera Indica (Mango) Fruit Extract, Passiflora Incarnata Fruit Extract, Plumeria Acutifolia Flower Extract, Psidium Guajava Fruit Extract, Panthenol, Aloe Barbadensis Leaf Juice, Sodium Ascorbyl Phosphate.

Other Information

• protect this product from excessive heat and direct sun

Questions or Comments?

Call 1-800-NO UV RAY, Mon-Fri

PRINCIPAL DISPLAY PANEL

HAWAIIAN
TROPIC®
SPORT SUNSCREEN LOTION
EVERYDAY
ACTIVE
SWEAT | WATER RESISTANT
(80 MINUTES)
50
DERM TESTED | VEGAN
BROAD SPECTRUM SPF 50 UVA/UVB
8 FL. OZ (236 mL)